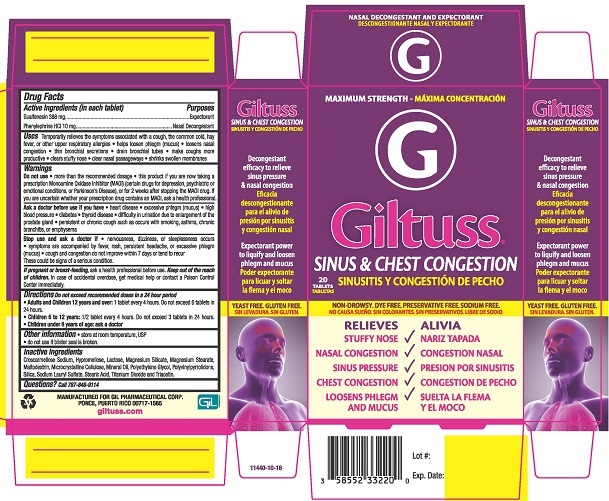 DRUG LABEL: Giltuss Sinus and Chest Congestion
NDC: 58552-332 | Form: TABLET
Manufacturer: Gil Pharmaceutical Corp
Category: otc | Type: HUMAN OTC DRUG LABEL
Date: 20251009

ACTIVE INGREDIENTS: GUAIFENESIN 388 mg/1 1; PHENYLEPHRINE HYDROCHLORIDE 10 mg/1 1
INACTIVE INGREDIENTS: STEARIC ACID; TITANIUM DIOXIDE; TRIACETIN; POLYETHYLENE GLYCOL 400; CROSCARMELLOSE SODIUM; HYPROMELLOSE, UNSPECIFIED; LACTOSE; MAGNESIUM STEARATE; MALTODEXTRIN; CELLULOSE, MICROCRYSTALLINE; LIGHT MINERAL OIL; POVIDONE K30; SILICON DIOXIDE; SODIUM LAURYL SULFATE; TALC

4062- Giltuss Sinus & Chest Congestion Tablets

Drug Facts

Active Ingredient (in each tablet)

Guaifenesin 388 mg

Phenylephrine HCl 10 mg

Purpose

Expectorant

Nasal Decongestant

Uses

temporarily relieves the symptoms associated with a cough, the common cold, hay fever, or other upper respiratory allergies

- helps loosen phlegm (mucus)
- loosens nasal congestion
- thin bronchial secretions
- drain bronchial tubes
- make coughs more productive
- clears stuffy nose
- clear nasal passageways
- shrinks swollen membranes

Warnings

Do not use

- more than the recommended dosage
- this product if you are now taking a prescription Monoamine Oxidase Inhibitor (MAOI) (certain drugs for depression, psychiatric or emotional conditions, or Parkinson’s Disease), or for 2 weeks after stopping the MAOI drug. If you are uncertain whether your prescription drug contains an MAOI, ask a health professional.

Ask a doctor before use if you have

- heart disease
- excessive phlegm (mucus)
- high blood pressure
- diabetes
- thyroid disease
- difficulty in urination due to enlargement of the prostate gland
- persistent or chronic cough such as occurs with smoking, asthma, chronic bronchitis, or emphysema

Stop use and ask a doctor if

- nervousness, dizziness, or sleeplessness occurs
- symptoms are accompanied by fever, rash, persistent headache, or excessive phlegm (mucus)
- cough and congestion do not improve within 7 days or tend to recur.

These could be signs of a serious condition.

PREGNANCY OR BREAST FEEDING

If pregnant or breast-feeding, ask a health professional before use.

KEEP OUT OF REACH OF CHILDREN

Keep out of the reach of children.In case of accidental overdose, get medical help or contact a Poison Control Center immediately.

Directions

Do not exceed recommended doses in a 24 hour period

- Adults and Children 12 years and over:1 tablet every 4 hours. Do not exceed 6 tablets in 24 hours.
- Children 6 to 12 years:1/2 tablet every 4 hours. Do not exceed 3 tablets in 24 hours
- Children under 6 years of age: ask a doctor

Other information

- store at room temperature, USP
- do not use if blister seal is broken

INACTIVE INGREDIENT

Inactive ingredientsCroscarmellose Sodium, Hypromellose, Lactose, Magnesium Silicate, Magnesium Stearate, Maltodextrin, Microcrystalline Cellulose, Mineral Oil, Polyethylene Glycol, Polyvinylpyrrolidone, Silica, Sodium Lauryl Sulfate, Stearic Acid, Titanium Dioxide and Triacetin.

Questions? Call 787-848-9114

MANUFACTURED FOR GIL PHARMACEUTICAL CORP.

PONCE, PUERTO RICO 00717-1565

giltuss.com

PACKAGE LABEL

MAXIMUM STRENGTH

GILTUSS®

SINUS & CHEST CONGESTION

20 TABLETS

NON-DROWSY. DYE FREE. PRESERVATIVE .SODIUM FREE

RELIEVES

- STUFFY NOSE
- NASAL CONGESTION
- SINUS PRESSURE
- CHEST CONGESTION
- LOOSENS PHLEGM AND MUCUS